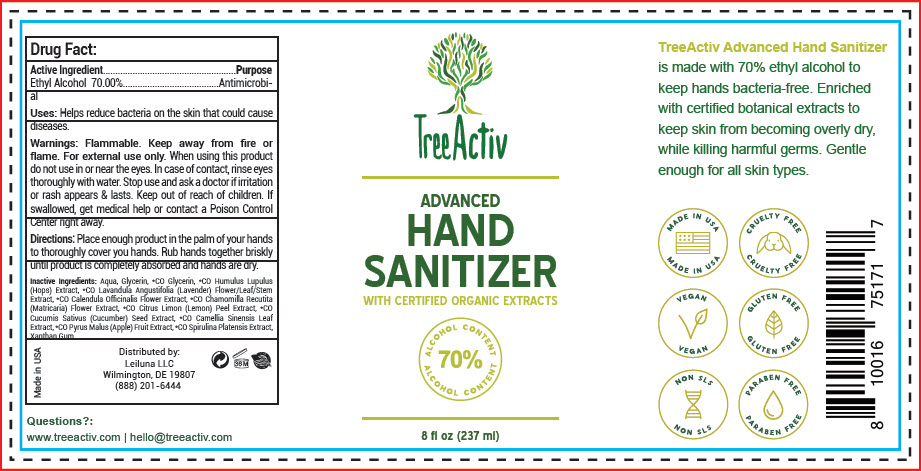 DRUG LABEL: TreeActiv Advanced Hand Sanitizer
NDC: 72841-301 | Form: GEL
Manufacturer: Leiluna LLC
Category: otc | Type: HUMAN OTC DRUG LABEL
Date: 20200424

ACTIVE INGREDIENTS: ALCOHOL 70 mL/100 mL
INACTIVE INGREDIENTS: WATER; GLYCERIN; HOPS; LAVANDULA ANGUSTIFOLIA SUBSP. ANGUSTIFOLIA FLOWERING TOP; CALENDULA OFFICINALIS FLOWER; CHAMOMILE; LEMON PEEL; CUCUMBER SEED; GREEN TEA LEAF; APPLE; ARTHROSPIRA PLATENSIS; XANTHAN GUM

TreeActiv Advanced Hand Sanitizer

Drug Fact:

Active Ingredient

Ethyl Alcohol 70.00%

Purpose

Antimicrobial

Uses

Helps reduce bacteria on the skin that could cause diseases.

Warnings

Flammable. Keep away from fire or flame. For external use only. When using this product do not use in or near the eyes. In case of contact, rinse eyes thoroughly with water. Stop use and ask a doctor if irritation or rash appears & lasts.

Keep out of reach of children. If swallowed, get medical help or contact a Poison Control Center right away.

Directions

Place enough product in the palm of your hands to thoroughly cover you hands. Rub hands together briskly until product is completely absorbed and hands are dry.

Inactive Ingredients

Aqua, Glycerin, *CO Glycerin, *CO Humulus Lupulus (Hops) Extract, *CO Lavandula Angustifolia (Lavender) Flower/Leaf/Stem Extract, *CO Calendula Officinalis Flower Extract, *CO Chamomilla Recutita (Matricaria) Flower Extract, *CO Citrus Limon (Lemon) Peel Extract, *CO Cucumis Sativus (Cucumber) Seed Extract, *CO Camellia Sinensis Leaf Extract, *CO Pyrus Malus (Apple) Fruit Extract, *CO Spirulina Platensis Extract, Xanthan Gum.

Questions?

www.treeactiv.com | hello@treeactiv.com

Distributed by:
Leiluna LLC
Wilmington, DE 19807

PRINCIPAL DISPLAY PANEL - 237 ml Bottle Label

TreeActiv

ADVANCED
HAND
SANITIZER

WITH CERTIFIED ORGANIC EXTRACTS

ALCOHOL CONTENT
70%

8 fl oz (237 ml)